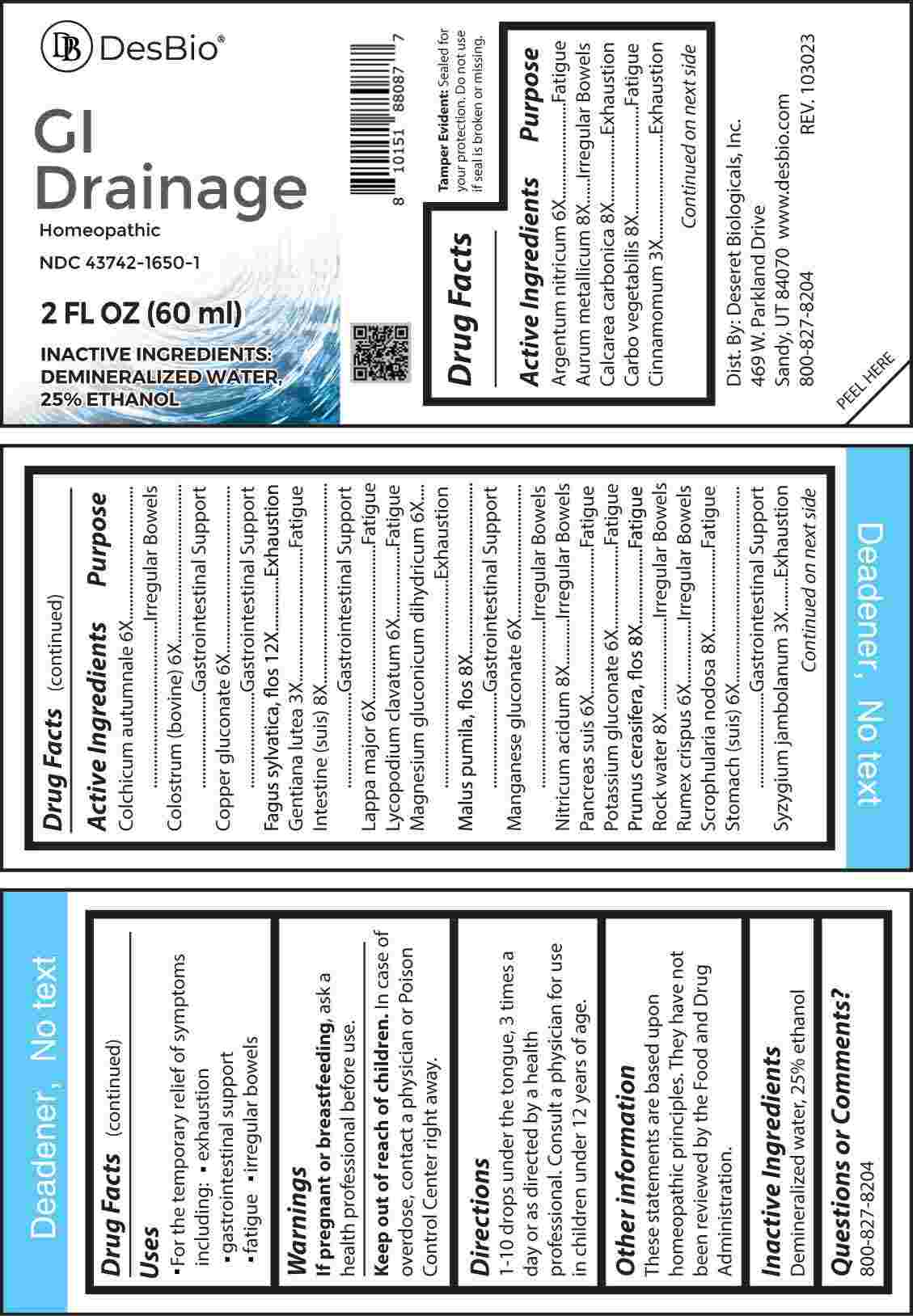 DRUG LABEL: GI Drainage
NDC: 43742-1650 | Form: LIQUID
Manufacturer: Deseret Biologicals, Inc.
Category: homeopathic | Type: HUMAN OTC DRUG LABEL
Date: 20240221

ACTIVE INGREDIENTS: CINNAMON 3 [hp_X]/1 mL; GENTIANA LUTEA ROOT 3 [hp_X]/1 mL; SYZYGIUM CUMINI SEED 3 [hp_X]/1 mL; SILVER NITRATE 6 [hp_X]/1 mL; COLCHICUM AUTUMNALE BULB 6 [hp_X]/1 mL; BOS TAURUS COLOSTRUM 6 [hp_X]/1 mL; COPPER GLUCONATE 6 [hp_X]/1 mL; ARCTIUM LAPPA ROOT 6 [hp_X]/1 mL; LYCOPODIUM CLAVATUM SPORE 6 [hp_X]/1 mL; MAGNESIUM GLUCONATE 6 [hp_X]/1 mL; MANGANESE GLUCONATE 6 [hp_X]/1 mL; SUS SCROFA PANCREAS 6 [hp_X]/1 mL; POTASSIUM GLUCONATE 6 [hp_X]/1 mL; RUMEX CRISPUS ROOT 6 [hp_X]/1 mL; SUS SCROFA STOMACH 6 [hp_X]/1 mL; GOLD 8 [hp_X]/1 mL; OYSTER SHELL CALCIUM CARBONATE, CRUDE 8 [hp_X]/1 mL; ACTIVATED CHARCOAL 8 [hp_X]/1 mL; PORK INTESTINE 8 [hp_X]/1 mL; MALUS PUMILA FLOWER 8 [hp_X]/1 mL; NITRIC ACID 8 [hp_X]/1 mL; PRUNUS CERASIFERA FLOWER 8 [hp_X]/1 mL; WATER 8 [hp_X]/1 mL; SCROPHULARIA NODOSA WHOLE 8 [hp_X]/1 mL; FAGUS SYLVATICA FLOWERING TOP 12 [hp_X]/1 mL
INACTIVE INGREDIENTS: ALCOHOL

DRUG FACTS:

ACTIVE INGREDIENTS:

Argentum Nitricum 6X, Aurum Metallicum 8X, Calcarea Carbonica 8X, Carbo Vegetabilis 8X, Cinnamomum 3X, Colchicum Autumnale 6X, Colostrum (Bovine) 6X, Copper Gluconate 6X, Fagus Sylvatica, Flos 12X, Gentiana Lutea 3X, Intestine (Suis) 8X, Lappa Major 6X, Lycopodium Clavatum 6X, Magnesium Gluconicum Dihydricum 6X, Malus Pumila, Flos 8X, Manganese Gluconate 6X, Nitricum Acidum 8X, Pancreas Suis 6X, Potassium Gluconate 6X, Prunus Cerasifera, Flos 8X, Rock Water 8X, Rumex Crispus 6X, Scrophularia Nodosa 8X, Stomach (Suis) 6X, Syzygium Jambolanum 3X.

PURPOSE:

Argentum Nitricum - Fatigue, Aurum Metallicum – Irregular Bowels, Calcarea Carbonica - Exhaustion, Carbo Vegetabilis - Fatigue, Cinnamomum - Exhaustion, Colchicum Autumnale – Irregular Bowels, Colostrum (Bovine) – Gastrointestinal Support, Copper Gluconate – Gastrointestinal Support, Fagus Sylvatica, Flos - Exhaustion, Gentiana Lutea - Fatigue, Intestine (Suis) – Gastrointestinal Support, Lappa Major - Fatigue, Lycopodium Clavatum - Fatigue, Magnesium Gluconicum Dihydricum - Exhaustion, Malus Pumila, Flos – Gastrointestinal Support, Manganese Gluconate – Irregular Bowels, Nitricum Acidum – Irregular Bowels, Pancreas Suis - Fatigue, Potassium Gluconate -
Fatigue, Prunus Cerasifera, Flos - Fatigue, Rock Water – Irregular Bowels, Rumex Crispus – Irregular Bowels, Scrophularia Nodosa - Fatigue, Stomach (Suis) – Gastrointestinal Support, Syzygium Jambolanum - Exhaustion

USES:

• For the temporary relief of the symptoms including:

• exhaustion • gastrointestinal support

• fatigue • irregular bowels

These statements are based upon homeopathic principles. They have not been reviewed by the Food and Drug Administration.

WARNINGS:

If pregnant or breast-feeding, ask a health professional before use.

Keep out of reach of children. In case of overdose, contact a physician or Poison Control Center right away.

Tamper Evident: Sealed for your protection. Do not use if seal is broken or missing.

KEEP OUT OF REACH OF CHILDREN:

In case of overdose, contact a physician or Poison Control Center right away.

DIRECTIONS:

1-10 drops under the tongue, 3 times a day or as directed by a health professional. Consult a physician for use in children under 12 years of age.

INACTIVE INGREDIENTS:

Demineralized water, 25% ethanol

QUESTIONS:

Dist. By: Deseret Biologicals, Inc.
469 W. Parkland Drive
Sandy, UT 84070

www.desbio.com

800-827-8204

PACKAGE LABEL DISPLAY:

Des Bio

GI Drainage

Homeopathic

NDC 43742-1650-1

2 FL OZ (60 ml)